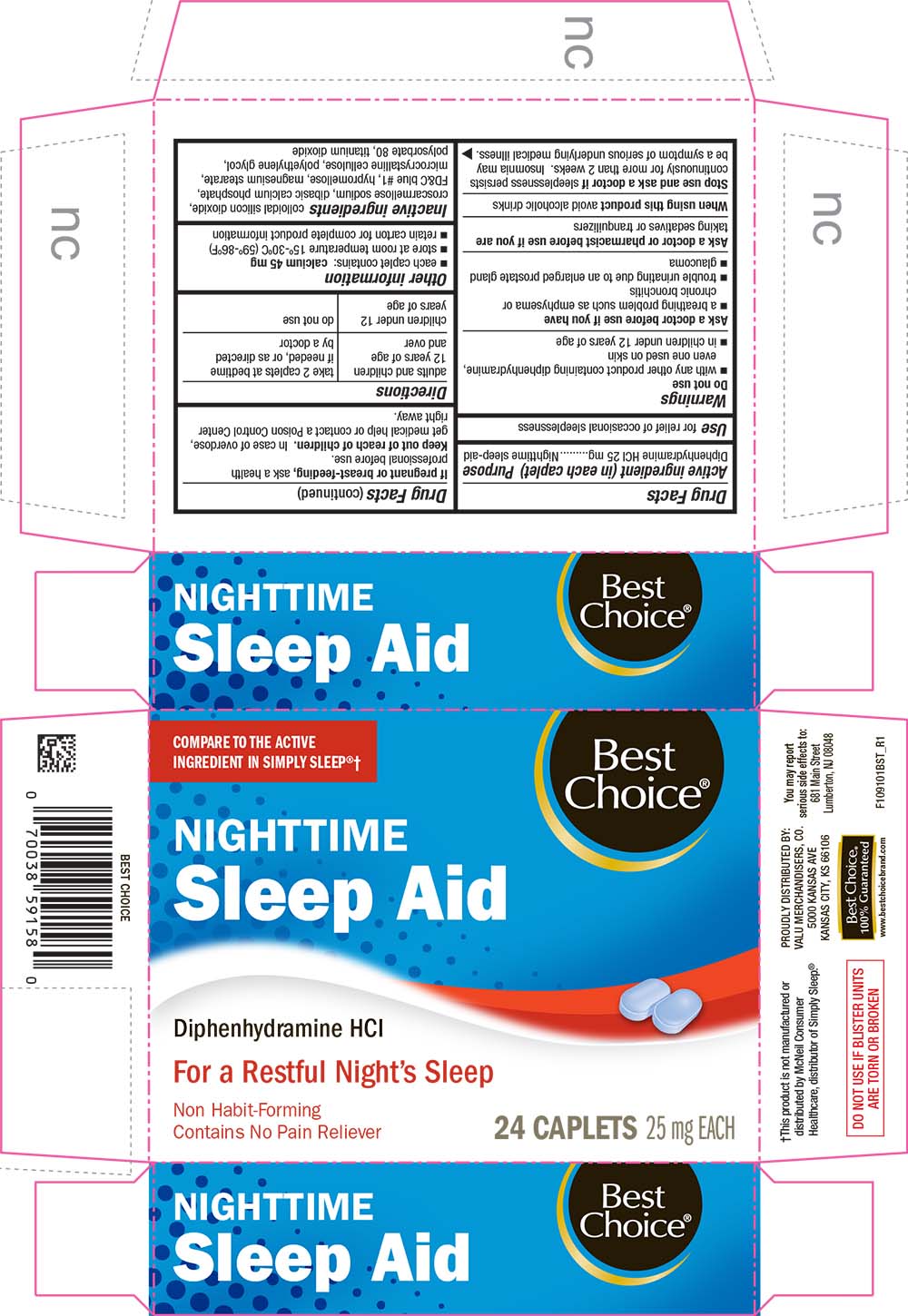 DRUG LABEL: Nighttime Sleep Aid
NDC: 63941-091 | Form: TABLET, COATED
Manufacturer: VALU MERCHANDISERS COMPANY
Category: otc | Type: HUMAN OTC DRUG LABEL
Date: 20251211

ACTIVE INGREDIENTS: DIPHENHYDRAMINE HYDROCHLORIDE 25 mg/1 1
INACTIVE INGREDIENTS: SILICON DIOXIDE; CROSCARMELLOSE SODIUM; CALCIUM PHOSPHATE, DIBASIC, ANHYDROUS; FD&C BLUE NO. 1; HYPROMELLOSES; MAGNESIUM STEARATE; CELLULOSE, MICROCRYSTALLINE; POLYETHYLENE GLYCOL, UNSPECIFIED; POLYSORBATE 80; TITANIUM DIOXIDE

1091-BST-2021-1116

Drug Facts

Active ingredient (in each caplet)

Diphenhydramine HCl 25 mg

Purpose

Nighttime sleep-aid

Use

for relief of occasional sleeplessness

Warnings

Do not use

- with any other product containing diphenhydramine, even one used on skin
- in children under 12 years of age

Ask a doctor before use if you have

- a breathing problem such as emphysema or chronic bronchitis
- trouble urinating due to an enlarged prostate gland
- glaucoma

Ask a doctor or pharmacist before use if you are taking sedatives or tranquilizers

When using this product avoid alcoholic drinks

Stop use and ask a doctor if sleeplessness persists continuously for more than 2 weeks. Insomnia may be a symptom of serious underlying medical illness.

PREGNANCY OR BREAST FEEDING

If pregnant or breast-feeding, ask a health professional before use.

Keep out of reach of children. In case of overdose, get medical help or contact a Poison Control Center right away.

Directions

adults and children 12 years of age and over | take 2 caplets at bedtime if needed, or as directed by a doctor
children under 12 years of age | do not use

Other information

- each caplet contains: calcium 45 mg
- store at room temperature 15°-30°C (59°-86°F)
- retain carton for complete product information

Inactive ingredients

colloidal silicon dioxide, croscarmellose sodium, dibasic calcium phosphate, FD&C blue #1, hypromellose, magnesium stearate, microcrystalline cellulose, polyethylene glycol, polysorbate 80, titanium dioxide

PRINCIPAL DISPLAY PANEL

COMPARE TO THE ACTIVE INGREDIENT IN SIMPLY SLEEP®†

Best Choice®

NIGHTTIME

Sleep Aid

Siphenhydramine HCl

For a Restful Night's Sleep

Non Habit-Forming

Contains No Pain Reliever

24 CAPLETS 25 mg EACH